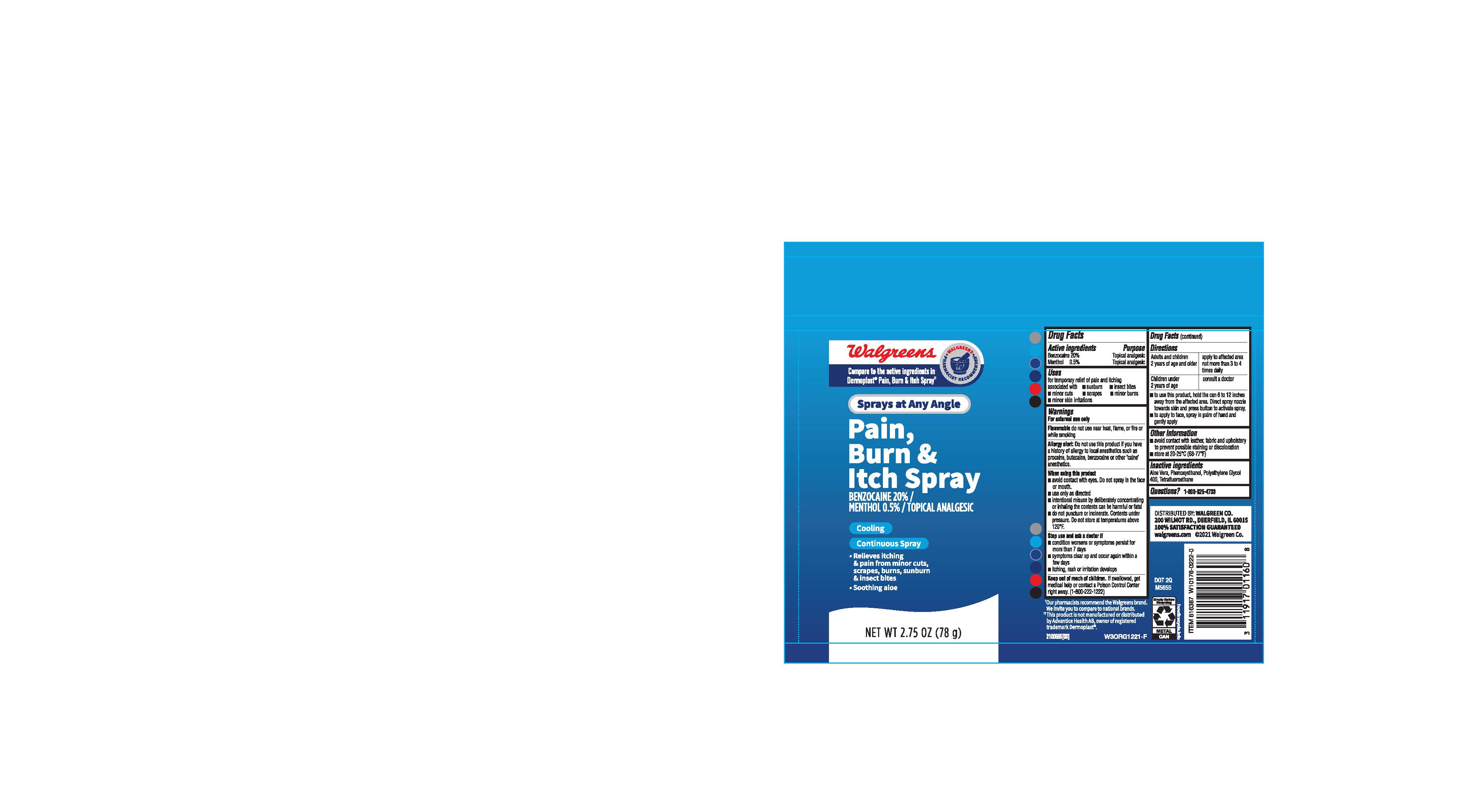 DRUG LABEL: Walgreens Pain Burn Itch Relief
NDC: 0363-2053 | Form: SPRAY
Manufacturer: Walgreens
Category: otc | Type: HUMAN OTC DRUG LABEL
Date: 20241211

ACTIVE INGREDIENTS: MENTHOL 5 mg/1 g; BENZOCAINE 200 mg/1 g
INACTIVE INGREDIENTS: PHENOXYETHANOL; ALOE VERA LEAF; NORFLURANE; POLYETHYLENE GLYCOL 400

Walgreens Pain Burn Itch Relief Spray

ACTIVE INGREDIENT

20% Benzocaine

0.5% Menthol

PURPOSE

Topical Analgesic

INDICATIONS AND USAGE

For temporary relief of pain and itching associated with :

- sunburn
- insect bites
- minor cuts
- scrapes
- minor burns
- minor skin irritations

WARNINGS

For External use only

DO NOT USE

Flamable:

- Do not use near heat, flame, or fire or while smoking

Allergy Alert:

- Do not use this product if you have a history of allergy to local anesthetics such as procaine, benzocaine or other "caine" anesthetics.

WHEN USING

Avoid contact with eyes. Do not spray in the face or mouth

Use only as ditected

Intentional misuse by delibrately concentrating or inhailing the contents can be harmful or fatal

Do not puncture or incinerate.Contents under pressure. Do not store at temperatures above 120°F.

Stop use and ask a doctor if

- condition worsens or symptoms persist for more than 7 days
- symptoms clear up and occur again within a few days
- itiching, rash or irritation develops

KEEP OUT OF REACH OF CHILDREN

If swallowed, get medical help or contact a Poision Control Center right away. (1-800-222-1222)

DOSAGE AND ADMINISTRATION

Adults and children 2 years of age and older : Apply to the affected area not more than 3 to 4 times daily

Children under 2 years of age: Cinsult a doctor

- To use this product, hold the can 6 to 12 inches away from the affected area. Direct spray nozzle towards skin and press button to activate spray.
- To apply to face, spray in palm of hand and gently apply.

OTHER SAFETY INFORMATION

- Avoid contact with leather, fabric and upholstery to prevent possible staining or discoloration
- Store at 20-25°C (68-77°F)

INACTIVE INGREDIENT

Aloe Vera, Phenoxyethanol, Polyethylene Glycol 400, Tetrafluoroethane

QUESTIONS

1-800-925-4733